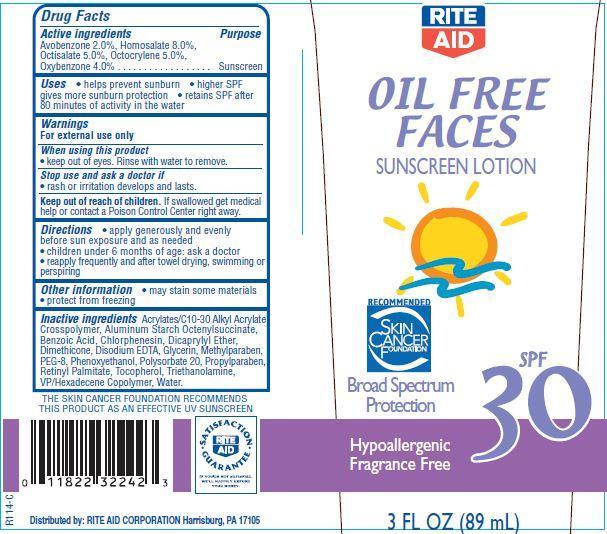 DRUG LABEL: Rite Aid Oil Free Faces Sunscreen
NDC: 11822-9003 | Form: LOTION
Manufacturer: RITE AID CORPORATION
Category: otc | Type: HUMAN OTC DRUG LABEL
Date: 20121121

ACTIVE INGREDIENTS: AVOBENZONE 2 g/100 g; HOMOSALATE 8 g/100 g; OCTISALATE 5 g/100 g; OCTOCRYLENE 5 g/100 g; OXYBENZONE 4 g/100 g
INACTIVE INGREDIENTS: WATER; BENZOIC ACID; CHLORPHENESIN; TROLAMINE; ALUMINUM STARCH OCTENYLSUCCINATE; DICAPRYLYL ETHER; GLYCERIN; DIMETHICONE; METHYLPARABEN; TOCOPHEROL; EDETATE DISODIUM; PROPYLPARABEN; POLYETHYLENE GLYCOL 400; PHENOXYETHANOL; POLYSORBATE 20; VITAMIN A PALMITATE

Drug Facts

Active Ingredients

Avobenzone 2.0 %

Homosalate 8.0%

Octisalate 5.0%

Octocrylene 5.0%

Oxybenzone 4.0%

Purpose

Sunscreen

Uses

- helps prevent sunburn
- higher SPF gives more sunburn protection
- retains SPF after 80 minutes of activity in the water

Warnings

For external use only

When using this product

- keep out of eyes. Rinse with water to remove.

stop use and ask a doctor if

- rash or irritation develops and lasts

keep out of reach of children.

If swallowed, get medical help or contact a Poison Control Center right away.

Directions

- apply generously and evenly before sun exposure and as needed
- children under 6 months of age:ask a doctor
- reapply frequently and after towel drying, swimming or perspiring.

Other Information

- may stain some materials
- protect from freezing

Inactive Ingredients

Water, Dicaprylyl Ether, PEG-8, VP/Hexadecene Copolymer, Aluminum Starch Octenylsuccinate, Dimethicone, Acrylates/C10-30 Alkyl Acrylate Crosspolymer, Triethanolamine, Polysorbate 20, Glycerin, Benzoic Acid, Disodium EDTA, Retinyl Palmitate, Tocopherol, Phenoxyethanol, Methylparaben, Chlorphenesin, Propylparaben.

Principal Display Panel

RITE
AID
OIL FREE
FACES
SUNSCREEN LOTION
SPF
30
RECOMMENDED
SKIN CANCER
FOUNDATION
Broad Spectrum
Protection
Hypoallergenic
Fragrance Free
3 FL OZ (89 mL)